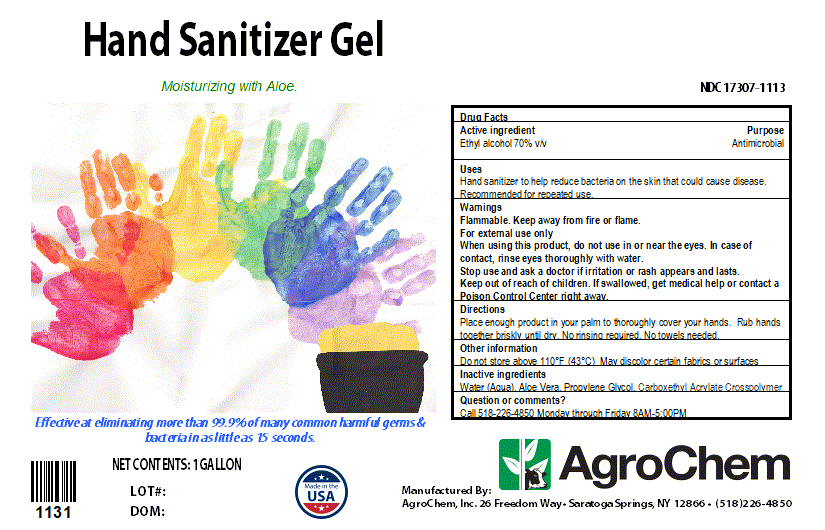 DRUG LABEL: Hand Sanitizer Gel
NDC: 17307-1113 | Form: LIQUID
Manufacturer: AgroChem Inc
Category: otc | Type: HUMAN OTC DRUG LABEL
Date: 20200402

ACTIVE INGREDIENTS: ALCOHOL 0.7 mL/1 mL
INACTIVE INGREDIENTS: ALOE VERA LEAF 0.005 mL/1 mL; PROPYLENE GLYCOL 0.02 mL/1 mL; AMMONIUM ACRYLOYLDIMETHYLTAURATE 0.0075 mL/1 mL; WATER 0.2675 mL/1 mL

Hand Sanitizer Gel

DESCRIPTION

Hand Sanitizer Gel

Moisturizing with Aloe

Effective at eliminating more than 99.9% of many common harmful germs & bacteria in as little as 15 seconds.

Active Ingredient(s)

Ethyl alcohol 70% v/v Purpose:Antimicrobial

Purpose

Antimicrobial, Hand Sanitizer

Use

Hand Sanitizer to help reduce bacteria that potentially can cause disease. Recommended for repeated use.

Warnings

For external use only. Flammable. Keep away from heat or flame

When using this product keep out of eyes, ears, and mouth. In case of contact with eyes, rinse eyes thoroughly with water.
Stop use and ask a doctor if irritation or rash occurs. These may be signs of a serious condition.
Keep out of reach of children. If swallowed, get medical help or contact a Poison Control Center right away.

Stop use and ask a doctor if irritation or rash occurs.

Keep out of reach of children. If swallowed, get medical help or contact a Poison Control Center right away.

Directions

- Place enough product on hands to cover all surfaces. Rub hands together until dry.
- No rinsing required. No towels needed.

Other information

Do not store above 110°F (43°C) May discolor certain fabrics or surfaces

Inactive ingredients

Water, Aloe Vera, Propylene Glycol, Carboxlethyl Acrylate Crosspolymer

3780 mL label